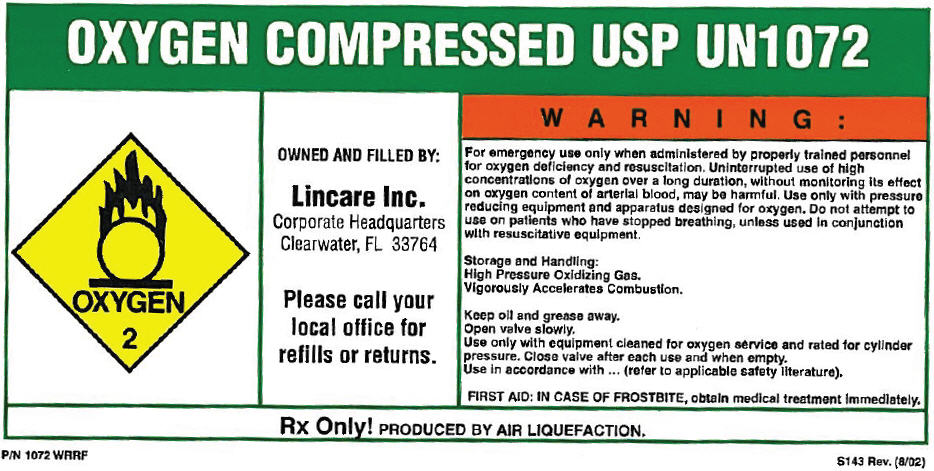 DRUG LABEL: Oxygen
NDC: 57800-001 | Form: GAS
Manufacturer: Lincare Inc.
Category: prescription | Type: HUMAN PRESCRIPTION DRUG LABEL
Date: 20251003

ACTIVE INGREDIENTS: OXYGEN 99 L/100 L

PRINCIPAL DISPLAY PANEL - Shipping Label

OXYGEN COMPRESSED USP UN1072

OXYGEN

2

OWNED AND FILLED BY:

Lincare Inc.
Corporate Headquarters
Clearwater, FL 33764

Please call your
local office for
refills or returns.

WARNING:

For emergency use only when administered by properly trained personnel
for oxygen deficiency and resuscitation. Uninterrupted use of high
concentrations of oxygen over a long duration, without monitoring its effect
on oxygen content of arterial blood, may be harmful. Use only with pressure
reducing equipment and apparatus designed for oxygen. Do not attempt to
use on patients who have stopped breathing, unless used in conjunction
with resuscitative equipment.

Storage and Handling:
High Pressure Oxidizing Gas.
Vigorously Accelerates Combustion.

Keep oil and grease away.
Open valve slowly.
Use only with equipment cleaned for oxygen service and rated for cylinder
pressure. Close valve after each use and when empty.
Use in accordance with ... (refer to applicable safety literature).

FIRST AID: IN CASE OF FROSTBITE, obtain medical treatment immediately.

Rx Only! PRODUCED BY AIR LIQUEFACTION.

P/N 1072 WRRF
S143 Rev. (8/02)